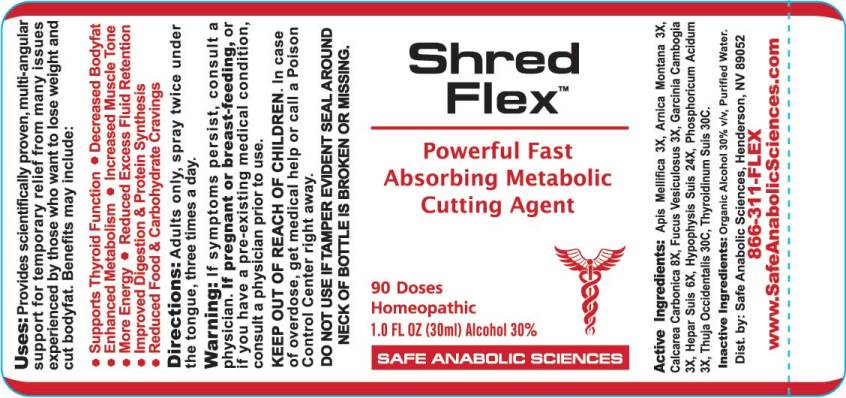 DRUG LABEL: Shred Flex
NDC: 49215-0010 | Form: SPRAY
Manufacturer: Safe Anabolic Sciences
Category: homeopathic | Type: HUMAN OTC DRUG LABEL
Date: 20180504

ACTIVE INGREDIENTS: APIS MELLIFERA 3 [hp_X]/1 mL; ARNICA MONTANA 3 [hp_X]/1 mL; OYSTER SHELL CALCIUM CARBONATE, CRUDE 8 [hp_X]/1 mL; FUCUS VESICULOSUS 3 [hp_X]/1 mL; GARCINIA CAMBOGIA FRUIT 3 [hp_X]/1 mL; PORK LIVER 6 [hp_X]/1 mL; SUS SCROFA PITUITARY GLAND 24 [hp_X]/1 mL; PHOSPHORIC ACID 3 [hp_X]/1 mL; THUJA OCCIDENTALIS LEAFY TWIG 30 [hp_C]/1 mL; SUS SCROFA THYROID 30 [hp_C]/1 mL
INACTIVE INGREDIENTS: WATER; ALCOHOL

Drug Facts:

ACTIVE INGREDIENTS:

Apis Mellifica 3X, Arnica Montana 3X, Calcarea Carbonica 8X, Fucus Vesiculosus 3X, Garcinia Cambogia 3X, Hepar Suis 6X, Hypophysis Suis 24X, Phosphoricum Acidum 3X, Thuja Occidentalis 30C, Thyroidinum (Suis) 30C.

USES:

Provides scientifically proven, multi-angular support for temporary relief from many issues experienced by those who want to lose weight and cut bodyfat. Benefits may include:

• Supports Thyroid Function • Decreased Bodyfat

• Enhanced Metabolism • Increased Muscle Tone

• More Energy • Reduced Excess Fluid Retention

• Improved Digestion & Protein Synthesis

• Reduced Food & Carbohydrate Cravings

WARNING:

If symptoms persist, consult a physician.

If pregnant or breast-feeding, or if you have a pre-existing medical condition, consult a physician prior to use.

KEEP OUT OF REACH OF CHILDREN. In case of overdose, get medical help or call a Poison Control Center right away.

DO NOT USE IF TAMPER EVIDENT SEAL AROUND NECK OF BOTTLE IS BROKEN OR MISSING.

KEEP OUT OF REACH OF CHILDREN. In case of overdose, get medical help or call a Poison Control Center right away.

DIRECTIONS:

Adults only, spray twice under the tongue, three times a day.

INDICATIONS:

Provides scientifically proven, multi-angular support for temporary relief from many issues experienced by those who want to lose weight and cut bodyfat. Benefits may include:

• Supports Thyroid Function • Decreased Bodyfat

• Enhanced Metabolism • Increased Muscle Tone

• More Energy • Reduced Excess Fluid Retention

• Improved Digestion & Protein Synthesis

• Reduced Food & Carbohydrate Cravings

INACTIVE INGREDIENTS:

Organic Alcohol 30% V/V, Purified Water

QUESTIONS:

Dist. by: Safe Anabolic Sciences, Henderson, NV 89052
866-311-FLEX
www.SafeAnabolicSciences.com

PACKAGE LABEL DISPLAY:

Shred

Flex

Powerful Fast
Absorbing Liquid
Anabolic Cutting Agent

90 Doses
Homeopathic
1.0 FL OZ (30 ml)

SAFE ANABOLIC SCIENCES